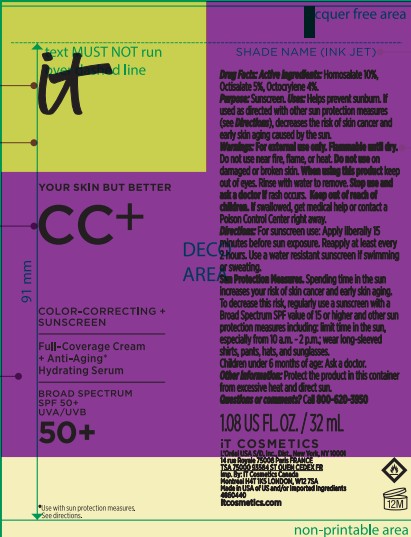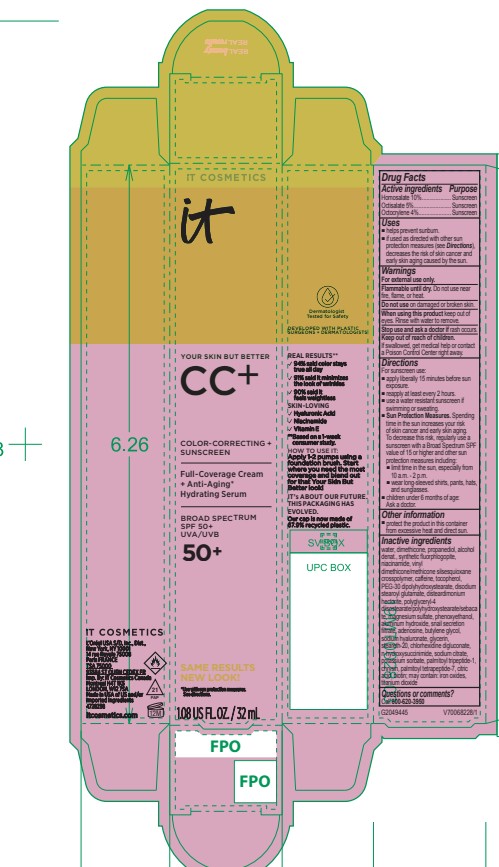 DRUG LABEL: IT Cosmetics Your Skin But Better CC Plus Color Correcting Broad Spectrum SPF 50 Plus Sunscreen Full Coverage Deep Deep Honey Deep Bronze Neutral Deep Deep Mocha Tan Cool Rich Cool Deep Cool Neutral Rich
NDC: 49967-904 | Form: CREAM
Manufacturer: L’Oreal USA Products Inc
Category: otc | Type: HUMAN OTC DRUG LABEL
Date: 20250630

ACTIVE INGREDIENTS: HOMOSALATE 100 mg/1 mL; OCTOCRYLENE 40 mg/1 mL; OCTISALATE 50 mg/1 mL
INACTIVE INGREDIENTS: WATER; DIMETHICONE; PROPANEDIOL; ALCOHOL; MAGNESIUM POTASSIUM ALUMINOSILICATE FLUORIDE; NIACINAMIDE; VINYL DIMETHICONE/METHICONE SILSESQUIOXANE CROSSPOLYMER; CAFFEINE; TOCOPHEROL; PEG-30 DIPOLYHYDROXYSTEARATE; DISODIUM STEAROYL GLUTAMATE; DISTEARDIMONIUM HECTORITE; POLYGLYCERYL-4 DIISOSTEARATE/POLYHYDROXYSTEARATE/SEBACATE; MAGNESIUM SULFATE; PHENOXYETHANOL; ALUMINUM HYDROXIDE; SNAIL SECRETION FILTRATE; ADENOSINE; BUTYLENE GLYCOL; SODIUM HYALURONATE; GLYCERIN; STEARETH-20; CHLORHEXIDINE DIGLUCONATE; N-HYDROXYSUCCINIMIDE; SODIUM CITRATE; POTASSIUM SORBATE; PALMITOYL TRIPEPTIDE-1; CHRYSIN; PALMITOYL TETRAPEPTIDE-7; CITRIC ACID; BIOTIN; FERRIC OXIDE RED; FERRIC OXIDE YELLOW

Drug Facts

Active ingredients

Homosalate 10%

Octisalate 5%

Octocrylene 4%

Purpose

Sunscreen

Uses

■ helps prevent sunburn.

■ if used as directed with other sun protection measures (see Directions), decreases the risk of skin cancer and early skin aging caused by the sun

Warnings

For external use only

Flammable until dry.

Do not use near fire, flame, or heat.

Do not use

on damaged or broken skin

When using this product

keep out of eyes. Rinse with water to remove.

Stop use and ask a doctor if

rash occurs

Keep out of reach of children.

If swallowed, get medical help or contact a Poison Control Center right away.

Directions

For sunscreen use:
■ apply liberally 15 minutes before sun exposure

■ reapply at least every 2 hours

■ use a water resistant sunscreen if swimming or sweating

■ Sun Protection Measures. Spending time in the sun increases your risk of skin cancer and early skin aging. To decrease this risk, regularly use a sunscreen with a Broad Spectrum SPF value of 15 or higher and other sun protection measures including:
■ limit time in the sun, especially from 10 a.m. - 2 p.m.
■ wear long-sleeved shirts, pants, hats, and sunglasses

■ children under 6 months of age: Ask a doctor

Other information

protect the product in this container from excessive heat and direct sun

Inactive ingredients

water, dimethicone, propanediol, alcohol denat., synthetic fluorphlogopite, niacinamide, vinyl dimethicone/methicone silsesquioxane crosspolymer, caffeine, tocopherol, PEG-30 dipolyhydroxystearate, disodium stearoyl glutamate, disteardimonium hectorite, polyglyceryl-4 diisostearate/polyhydroxystearate/sebacate, magnesium sulfate, phenoxyethanol, aluminum hydroxide, snail secretion filtrate, adenosine, butylene glycol, sodium hyaluronate, glycerin, steareth-20, chlorhexidine digluconate, n-hydroxysuccinimide, sodium citrate, potassium sorbate, palmitoyl tripeptide-1, chrysin, palmitoyl tetrapeptide-7, citric acid, biotin; may contain: iron oxides, titanium dioxide

Questions or comments?

Call 800-620-3950